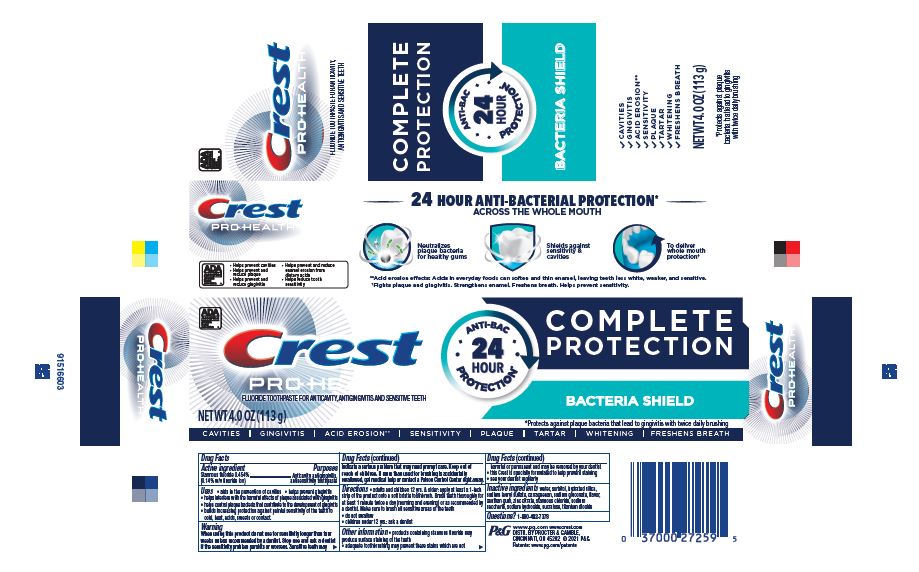 DRUG LABEL: Crest Pro-Health
NDC: 69423-916 | Form: PASTE, DENTIFRICE
Manufacturer: The Procter & Gamble Manufacturing Company
Category: otc | Type: HUMAN OTC DRUG LABEL
Date: 20250806

ACTIVE INGREDIENTS: STANNOUS FLUORIDE 1.4 mg/1 g
INACTIVE INGREDIENTS: SUCRALOSE; STANNOUS CHLORIDE; WATER; HYDRATED SILICA; CARRAGEENAN; SODIUM GLUCONATE; XANTHAN GUM; ZINC CITRATE; SODIUM LAURYL SULFATE; SORBITOL; SODIUM HYDROXIDE; SACCHARIN SODIUM; TITANIUM DIOXIDE

Crest Pro-Health Complete Protection Bacteria Shield

Drug Facts

Active ingredient

Stannous fluoride 0.454%

(0.14% w/v fluoride ion)

Purposes

Anticavity, antigingivitis, antisensitivity toothpaste

Uses

- aids in the prevention of cavities
- helps prevent gingivitis
- helps interfere with the harmful effects of plaque associated with gingivitis
- helps control plaque bacteria that contribute to the development of gingivitis
- builds increasing protection against painful sensitivity of the teeth to cold, heat, acids, sweets or contact.

Warning

When using this product do not use for sensitivity longer than four weeks unless recommended by a dentist. Stop use and ask a dentist if the sensitivity problem persists or worsens. Sensitive teeth may indicate a serious problem that may need prompt care.

Keep out of reach of children under 12 yrs. of age. If more than used for brushing is accidentally swallowed, get medical help or contact a Poison Control Center right away.

Directions

- adults and children 12 yrs. & older: apply at least a 1-inch strip of the product onto a soft bristle toothbrush. Brush teeth thoroughly for at least 1 minute twice a day (morning and evening) or as recommended by a dentist. Make sure to brush all sensitive areas of the teeth
- do not swallow
- children under 12 yrs. of age: ask a dentist

Other information

- products containing stannous fluoride may produce surface staining of the teeth
- adequate toothbrushing may prevent these stains which are not harmful or permanent and may be removed by your dentist
- this Crest is specially formulated to help prevent staining
- see your dentist regularly

Inactive ingredients

water, sorbitol, hydrated silica, sodium lauryl sulfate, carrageenan, sodium gluconate, flavor, xanthan gum, zinc citrate, stannous chloride, sodium saccharin, sodium hydroxide, sucralose, titanium dioxide

Questions?

1-800-492-7378

DISTR. BY PROCTER & GAMBLE,

CINCINNATI, OH 45202

Principal Display Panel - 113 g tube in carton

Crest®

PRO-HEALTH™

FLUORIDE TOOTHPASTE FOR ANTICAVITY, ANTIGINGIVITIS AND SENSITIVE TEETH

NET WT 4.0 OZ (113 g)

CAVITIES GINGIVITIS ACID EROSION** SENSITIVITY PLAQUE TARTAR WHITENING FRESHENS BREATH

ANTI-BAC 24 HOUR PROTECTION*

COMPLETE PROTECTION

BACTERIA SHIELD

*Protects against plaque bacteria that lead to gingivitis with twice daily brushing